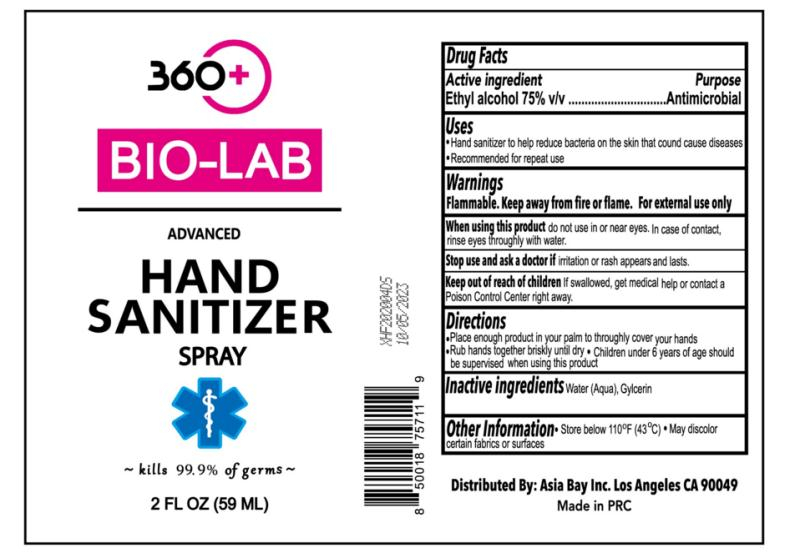 DRUG LABEL: Wash-free hand sanitizer
NDC: 55028-012 | Form: SPRAY
Manufacturer: Zhongshan Dermey Commodity Co., Ltd.
Category: otc | Type: HUMAN OTC DRUG LABEL
Date: 20200717

ACTIVE INGREDIENTS: ALCOHOL 44.25 mL/59 mL
INACTIVE INGREDIENTS: TROLAMINE; GLYCERIN; CARBOMER HOMOPOLYMER, UNSPECIFIED TYPE; WATER

DOSAGE AND ADMINISTRATION

Keep away from heat and flame.

INACTIVE INGREDIENT

Water

Glycerin

Carbomer

Triethanolamine

INDICATIONS AND USAGE

Squeeze 3-4 drops each time on palm，then gently rub evenly to clean and disinfect the surface of the hands, and rub until dry.

ACTIVE INGREDIENT

Alcohol

keep out of children

WARNINGS

Avoid direct contact with eyes and damaged skin. This product is for external use.